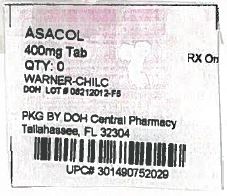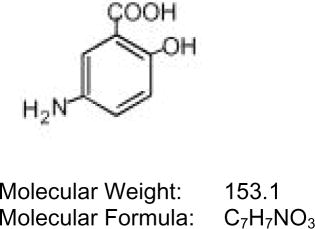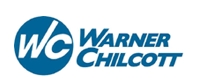 DRUG LABEL: ASACOL
NDC: 53808-0823 | Form: TABLET, DELAYED RELEASE
Manufacturer: State of Florida DOH Central Pharmacy
Category: prescription | Type: HUMAN PRESCRIPTION DRUG LABEL
Date: 20140307

ACTIVE INGREDIENTS: MESALAMINE 400 mg/1 1
INACTIVE INGREDIENTS: SILICON DIOXIDE; DIBUTYL PHTHALATE; FERRIC OXIDE RED; FERRIC OXIDE YELLOW; LACTOSE MONOHYDRATE; MAGNESIUM STEARATE; METHACRYLIC ACID - METHYL METHACRYLATE COPOLYMER (1:2); POLYETHYLENE GLYCOLS; POVIDONE; SODIUM STARCH GLYCOLATE TYPE A POTATO; TALC

Asacol®
(mesalamine)
Delayed-Release Tablets

DESCRIPTION:

Each Asacol® delayed-release tablet for oral administration contains 400 mg of mesalamine, an anti-inflammatory drug. The Asacol delayed-release tablets are coated with acrylic based resin, Eudragit S (methacrylic acid copolymer B, NF), which dissolves at pH 7 or greater, releasing mesalamine in the terminal ileum and beyond for topical anti-inflammatory action in the colon. Mesalamine has the chemical name 5-amino-2-hydroxybenzoic acid; its structural formula is:

Inactive Ingredients: Each tablet contains colloidal silicon dioxide, dibutyl phthalate, edible black ink, iron oxide red, iron oxide yellow, lactose monohydrate, magnesium stearate, methacrylic acid copolymer B (Eudragit S), polyethylene glycol, povidone, sodium starch glycolate, and talc.

CLINICAL PHARMACOLOGY:

Mesalamine is thought to be the major therapeutically active part of the sulfasalazine molecule in the treatment of ulcerative colitis. Sulfasalazine is converted to equimolar amounts of sulfapyridine and mesalamine by bacterial action in the colon. The usual oral dose of sulfasalazine for active ulcerative colitis is 3 to 4 grams daily in divided doses, which provides 1.2 to 1.6 grams of mesalamine to the colon.

The mechanism of action of mesalamine (and sulfasalazine) is unknown, but appears to be topical rather than systemic. Mucosal production of arachidonic acid (AA) metabolites, both through the cyclooxygenase pathways, i.e., prostanoids, and through the lipoxygenase pathways, i.e., leukotrienes (LTs) and hydroxyeicosatetraenoic acids (HETEs), is increased in patients with chronic inflammatory bowel disease, and it is possible that mesalamine diminishes inflammation by blocking cyclooxygenase and inhibiting prostaglandin (PG) production in the colon.

Pharmacokinetics:

Asacol tablets are coated with an acrylic-based resin that delays release of mesalamine until it reaches the terminal ileum and beyond. This has been demonstrated in human studies conducted with radiological and serum markers. Approximately 28% of the mesalamine in Asacol tablets is absorbed after oral ingestion, leaving the remainder available for topical action and excretion in the feces. Absorption of mesalamine is similar in fasted and fed subjects. The absorbed mesalamine is rapidly acetylated in the gut mucosal wall and by the liver. It is excreted mainly by the kidney as N-acetyl-5-aminosalicylic acid.

Mesalamine from orally administered Asacol tablets appears to be more extensively absorbed than the mesalamine released from sulfasalazine. Maximum plasma levels of mesalamine and N-acetyl-5-aminosalicylic acid following multiple Asacol doses are about 1.5 to 2 times higher than those following an equivalent dose of mesalamine in the form of sulfasalazine. Combined mesalamine and N-acetyl-5-aminosalicylic acid AUC’s and urine drug dose recoveries following multiple doses of Asacol tablets are about 1.3 to 1.5 times higher than those following an equivalent dose of mesalamine in the form of sulfasalazine.

The tmax for mesalamine and its metabolite, N-acetyl-5-aminosalicylic acid, is usually delayed, reflecting the delayed release, and ranges from 4 to 12 hours. The half-lives of elimination (t1/2elm) for mesalamine and N-acetyl-5-aminosalicylic acid are usually about 12 hours, but are variable, ranging from 2 to 15 hours. There is a large intersubject variability in the plasma concentrations of mesalamine and N-acetyl-5-aminosalicylic acid and in their elimination half-lives following administration of Asacol tablets.

Mildly to moderately active ulcerative colitis:

Two placebo-controlled studies have demonstrated the efficacy of Asacol tablets in patients with mildly to moderately active ulcerative colitis. In one randomized, double-blind, multi-center trial of 158 patients, Asacol doses of 1.6 g/day and 2.4 g/day were compared to placebo. At the dose of 2.4 g/day, Asacol tablets reduced the disease activity, with 21 of 43 (49%) Asacol patients showing improvement in sigmoidoscopic appearance of the bowel compared to 12 of 44 (27%) placebo patients (p = 0.048). In addition, significantly more patients in the Asacol 2.4 g/day group showed improvement in rectal bleeding and stool frequency. The 1.6 g/day dose did not produce consistent evidence of effectiveness.

In a second randomized, double-blind, placebo-controlled clinical trial of 6 weeks duration in 87 ulcerative colitis patients, Asacol tablets, at a dose of 4.8 g/day, gave sigmoidoscopic improvement in 28 of 38 (74%) patients compared to 10 of 38 (26%) placebo patients (p < 0.001). Also, more patients in the Asacol 4.8 g/day group showed improvement in overall symptoms.

Maintenance of remission of ulcerative colitis:

A 6-month, randomized, double-blind, placebo-controlled, multi-center study involved 264 patients treated with Asacol 0.8 g/day (n = 90), 1.6 g/day (n = 87), or placebo (n = 87). The proportion of patients treated with 0.8 g/day who maintained endoscopic remission was not statistically significant compared to placebo. In the intention to treat (ITT) analysis of all 174 patients treated with Asacol 1.6 g/day or placebo, Asacol maintained endoscopic remission of ulcerative colitis in 61 of 87 (70.1%) of patients, compared to 42 of 87 (48.3%) of placebo recipients (p = 0.005).

A pooled efficacy analysis of 4 maintenance trials compared Asacol, at doses of 0.8 g/day to 2.8 g/day, with sulfasalazine, at doses of 2 g/day to 4 g/day (n = 200). Treatment success was 59 of 98 (59%) for Asacol and 70 of 102 (69%) for sulfasalazine, a non-significant difference.

Study to assess the effect on male fertility:

The effect of Asacol (mesalamine) on sulfasalazine-induced impairment of male fertility was examined in an open-label study. Nine patients (age < 40 years) with chronic ulcerative colitis in clinical remission on sulfasalazine 2 g/day to 3 g/day were crossed over to an equivalent Asacol dose (0.8 g/day to 1.2 g/day) for 3 months. Improvement in sperm count (p < 0.02) and morphology (p < 0.02) occurred in all cases. Improvement in sperm motility (p < 0.001) occurred in 8 of the 9 patients.

INDICATIONS AND USAGE:

Asacol tablets are indicated for the treatment of mildly to moderately active ulcerative colitis and for the maintenance of remission of ulcerative colitis.

CONTRAINDICATIONS:

Asacol tablets are contraindicated in patients with hypersensitivity to salicylates or to any of the components of the Asacol tablet.

PRECAUTIONS:

General:

Patients with pyloric stenosis may have prolonged gastric retention of Asacol tablets which could delay release of mesalamine in the colon.

Exacerbation of the symptoms of colitis has been reported in 3% of Asacol-treated patients in controlled clinical trials. This acute reaction, characterized by cramping, abdominal pain, bloody diarrhea, and occasionally by fever, headache, malaise, pruritus, rash, and conjunctivitis, has been reported after the initiation of Asacol tablets as well as other mesalamine products. Symptoms usually abate when Asacol tablets are discontinued.

Some patients who have experienced a hypersensitivity reaction to sulfasalazine may have a similar reaction to Asacol tablets or to other compounds which contain or are converted to mesalamine.

Renal:

Renal impairment, including minimal change nephropathy, acute and chronic interstitial nephritis, and, rarely, renal failure has been reported in patients taking Asacol tablets as well as other compounds which contain or are converted to mesalamine. In animal studies (rats, dogs), the kidney is the principal target organ for toxicity. At doses of approximately 750 mg/kg to 1000 mg/kg [15 to 20 times the administered recommended human dose (based on a 50 kg person) on a mg/kg basis and 3 to 4 times on a mg/m^2 basis], mesalamine causes renal papillary necrosis. Therefore, caution should be exercised when using Asacol (or other compounds which contain or are converted to mesalamine or its metabolites) in patients with known renal dysfunction or history of renal disease. It is recommended that all patients have an evaluation of renal function prior to initiation of Asacol tablets and periodically while on Asacol therapy.

Use in Hepatic Impairment:

There have been reports of hepatic failure in patients with pre-existing liver disease who have been administered mesalamine. Caution should be exercised when administering Asacol to patients with liver disease.

Information for Patients:

Patients should be instructed to swallow the Asacol tablets whole, taking care not to break, cut, or chew the tablets, because the coating is an important part of the delayed-release formulation. In 2% to 3% of patients in clinical studies, intact or partially intact tablets have been reported in the stool. If this occurs repeatedly, patients should contact their physician.

Patients with ulcerative colitis should be made aware that ulcerative colitis rarely remits completely, and that the risk of relapse can be substantially reduced by continued administration of Asacol at a maintenance dosage.

Drug Interactions:

There are no known drug interactions.

Carcinogenesis, Mutagenesis, Impairment of Fertility:

Dietary mesalamine was not carcinogenic in rats at doses as high as 480 mg/kg/day, or in mice at 2000 mg/kg/day. These doses are 2.4 and 5.1 times the maximum recommended human maintenance dose of Asacol of 1.6 g/day (32 mg/kg/day if 50 kg body weight assumed or 1184 mg/m^2), respectively, based on body surface area. Mesalamine was negative in the Ames assay for mutagenesis, negative for induction of sister chromatid exchanges (SCE) and chromosomal aberrations in Chinese hamster ovary cells in vitro, and negative for induction of micronuclei (MN) in mouse bone marrow polychromatic erythrocytes. Mesalamine, at oral doses up to 480 mg/kg/day (about 1.6 times the recommended human treatment dose on a body surface area basis), was found to have no effect on fertility or reproductive performance of male and female rats.

Pregnancy:

Pregnancy Category C: There are no adequate and well controlled studies of Asacol use in pregnant women. Limited published human data on mesalamine show no increase in the overall rate of congenital malformations. Some data show an increased rate of preterm birth, stillbirth, and low birth weight; however, these adverse pregnancy outcomes are also associated with active inflammatory bowel disease. Animal reproduction studies of mesalamine found no evidence of fetal harm. However, dibutyl phthalate (DBP) is an inactive ingredient in Asacol’s enteric coating, and in animal studies at doses >190 times the human dose based on body surface area, maternal DBP was associated with external and skeletal malformations and adverse effects on the male reproductive system. Asacol should be used during pregnancy only if the potential benefit justifies the potential risk to the fetus.

Mesalamine crosses the placenta. In prospective and retrospective studies of over 600 women exposed to mesalamine during pregnancy, the observed rate of congenital malformations was not increased above the background rate in the general population. Some data show an increased rate of preterm birth, stillbirth, and low birth weight, but it is unclear whether this was due to underlying maternal disease, drug exposure, or both, as active inflammatory bowel disease is also associated with adverse pregnancy outcomes.

Reproduction studies with mesalamine were performed during organogenesis in rats and rabbits at oral doses up to 480 mg/kg/day. There was no evidence of impaired fertility or harm to the fetus. These mesalamine doses were about 1.6 times (rat) and 3.2 times (rabbit) the recommended human dose, based on body surface area.

Dibutyl phthalate (DBP) is an inactive ingredient in Asacol’s enteric coating. The human daily intake of DBP from the maximum recommended dose of Asacol tablets is about 21 mg. Published reports in rats show that male rat offspring exposed in utero to DBP (≥100 mg/kg/day, approximately 39 times the human dose based on body surface area), display reproductive system aberrations compatible with disruption of androgenic dependent development. The clinical significance of this finding in rats is unknown. At higher dosages (≥500 mg/kg/day, approximately 194 times the human dose based on body surface area), additional effects, including cryptorchidism, hypospadias, atrophy or agenesis of sex accessory organs, testicular injury, reduced daily sperm production, permanent retention of nipples, and decreased anogenital distance are noted. Female offspring are unaffected. High doses of DBP, administered to pregnant rats was associated with increased incidences of developmental abnormalities, such as cleft palate (≥630 mg/kg/day, about 244 times the human dose, based on body surface area) and skeletal abnormalities (≥750 mg/kg/day, about 290 times the human dose based on body surface area) in the offspring.

Nursing Mothers:

Mesalamine and its N-acetyl metabolite are excreted into human milk. In published lactation studies, maternal mesalamine doses from various oral and rectal formulations and products ranged from 500 mg to 3 g daily. The concentration of mesalamine in milk ranged from non-detectable to 0.11 mg/L. The concentration of the N-acetyl-5-aminosalicylic acid metabolite ranged from 5 to 18.1 mg/L. Based on these concentrations, estimated infant daily doses for an exclusively breastfed infant are 0 to 0.017 mg/kg/day of mesalamine and 0.75 to 2.72 mg/kg/day of N-acetyl-5-aminosalicylic acid. Caution should be exercised when Asacol is administered to a nursing woman.

Dibutyl phthalate (DBP), an inactive ingredient in the enteric coating of Asacol tablets, and its primary metabolite mono-butyl phthalate (MBP) are excreted into human milk. In pregnant rats, DBP causes fetal reproductive system aberrations/malformations in male offspring [see PRECAUTIONS, Pregnancy]. The clinical significance of this has not been determined.

Pediatric Use:

Safety and effectiveness of Asacol tablets in pediatric patients have not been established.

Geriatric Use:

Clinical studies of Asacol did not include sufficient numbers of subjects aged 65 and over to determine whether they respond differently from younger subjects. Other reported clinical experience has not identified differences in responses between the elderly and younger patients. In general, the greater frequency of decreased hepatic, renal, or cardiac function, and of concomitant disease or other drug therapy in elderly patients should be considered when prescribing Asacol. Reports from uncontrolled clinical studies and post-marketing reporting systems suggest a higher incidence of blood dyscrasias, i.e., agranulocytosis, neutropenia, pancytopenia, in subjects receiving Asacol who are 65 years or older. Caution should be taken to closely monitor blood cell counts during drug therapy.

This drug is known to be substantially excreted by the kidney, and the risk of toxic reactions to this drug may be greater in patients with impaired renal function. Because elderly patients are more likely to have decreased renal function, care should be taken when prescribing this drug therapy. As stated in the PRECAUTIONS section, it is recommended that all patients have an evaluation of renal function prior to initiation of Asacol tablets and periodically while on Asacol therapy.

ADVERSE REACTIONS:

Asacol tablets have been evaluated in 3685 inflammatory bowel disease patients (most patients with ulcerative colitis) in controlled and open-label studies. Adverse events seen in clinical trials with Asacol tablets have generally been mild and reversible. Adverse events presented in the following sections may occur regardless of length of therapy and similar events have been reported in short- and long-term studies and in the post-marketing setting.

In two short-term (6 weeks) placebo-controlled clinical studies involving 245 patients, 155 of whom were randomized to Asacol tablets, five (3.2%) of the Asacol patients discontinued Asacol therapy because of adverse events as compared to two (2.2%) of the placebo patients. Adverse reactions leading to withdrawal from Asacol tablets included (each in one patient): diarrhea and colitis flare; dizziness, nausea, joint pain, and headache; rash, lethargy and constipation; dry mouth, malaise, lower back discomfort, mild disorientation, mild indigestion and cramping; headache, nausea, aching, vomiting, muscle cramps, a stuffy head, plugged ears, and fever.

Adverse events occurring in Asacol-treated patients at a frequency of 2% or greater in the two short-term, double-blind, placebo-controlled trials mentioned above are listed in Table 1 below. Overall, the incidence of adverse events seen with Asacol tablets was similar to placebo.

Table 1 Frequency (%) of Common Adverse Events Reported in Ulcerative Colitis Patients Treated with Asacol Tablets or Placebo in Short-Term (6-Week) Double-Blind Controlled Studies
 | Percent of Patients with Adverse Events
 | Placebo | Asacol tablets
Event | (n = 87) | (n = 152)
Headache | 36 | 35
Abdominal pain | 14 | 18
Eructation | 15 | 16
Pain | 8 | 14
Nausea | 15 | 13
Pharyngitis | 9 | 11
Dizziness | 8 | 8
Asthenia | 15 | 7
Diarrhea | 9 | 7
Back pain | 5 | 7
Fever | 8 | 6
Rash | 3 | 6
Dyspepsia | 1 | 6
Rhinitis | 5 | 5
Arthralgia | 3 | 5
Hypertonia | 3 | 5
Vomiting | 2 | 5
Constipation | 1 | 5
Flatulence | 7 | 3
Dysmenorrhea | 3 | 3
Chest pain | 2 | 3
Chills | 2 | 3
Flu syndrome | 2 | 3
Peripheral edema | 2 | 3
Myalgia | 1 | 3
Sweating | 1 | 3
Colitis exacerbation | 0 | 3
Pruritus | 0 | 3
Acne | 1 | 2
Increased cough | 1 | 2
Malaise | 1 | 2
Arthritis | 0 | 2
Conjunctivitis | 0 | 2
Insomnia | 0 | 2

Of these adverse events, only rash showed a consistently higher frequency with increasing Asacol dose in these studies.

In a 6-month placebo-controlled maintenance trial involving 264 patients, 177 of whom were randomized to Asacol tablets, six (3.4%) of the Asacol patients discontinued Asacol therapy because of adverse events, as compared to four (4.6%) of the placebo patients. Adverse reactions leading to withdrawal from Asacol tablets included (each in one patient): anxiety; headache; pruritus; decreased libido; rheumatoid arthritis; and stomatitis and asthenia.

In the 6-month placebo-controlled maintenance trial, the incidence of adverse events seen with Asacol tablets was similar to that seen with placebo. In addition to events listed in Table 1, the following adverse events occurred in Asacol-treated patients at a frequency of 2% or greater in this study: abdominal enlargement, anxiety, bronchitis, ear disorder, ear pain, gastroenteritis, gastrointestinal hemorrhage, infection, joint disorder, migraine, nervousness, paresthesia, rectal disorder, rectal hemorrhage, sinusitis, stool abnormalities, tenesmus, urinary frequency, vasodilation, and vision abnormalities.

In 3342 patients in uncontrolled clinical studies, the following adverse events occurred at a frequency of 5% or greater and appeared to increase in frequency with increasing dose: asthenia, fever, flu syndrome, pain, abdominal pain, back pain, flatulence, gastrointestinal bleeding, arthralgia, and rhinitis.

In addition to the adverse events listed above, the following events have been reported in clinical studies, literature reports, and postmarketing use of products which contain (or have been metabolized to) mesalamine. Because many of these events were reported voluntarily from a population of unknown size, estimates of frequency cannot be made. These events have been chosen for inclusion due to their seriousness or potential causal connection to mesalamine:

Body as a Whole: Neck pain, facial edema, edema, lupus-like syndrome, drug fever (rare).

Cardiovascular: Pericarditis (rare), myocarditis (rare).

Gastrointestinal: Anorexia, pancreatitis, gastritis, increased appetite, cholecystitis, dry mouth, oral ulcers, perforated peptic ulcer (rare), bloody diarrhea. There have been rare reports of hepatotoxicity including, jaundice, cholestatic jaundice, hepatitis, and possible hepatocellular damage including liver necrosis and liver failure. Some of these cases were fatal. Asymptomatic elevations of liver enzymes which usually resolve during continued use or with discontinuation of the drug have also been reported. One case of Kawasaki-like syndrome which included changes in liver enzymes was also reported.

Hematologic: Agranulocytosis (rare), aplastic anemia (rare), thrombocytopenia, eosinophilia, leukopenia, anemia, lymphadenopathy.

Musculoskeletal: Gout.

Nervous: Depression, somnolence, emotional lability, hyperesthesia, vertigo, confusion, tremor, peripheral neuropathy (rare), transverse myelitis (rare), Guillain-Barré syndrome (rare).

Respiratory/Pulmonary: Eosinophilic pneumonia, interstitial pneumonitis, asthma exacerbation, pleuritis.

Skin: Alopecia, psoriasis (rare), pyoderma gangrenosum (rare), dry skin, erythema nodosum, urticaria.

Special Senses: Eye pain, taste perversion, blurred vision, tinnitus.

Urogenital: Renal Failure (rare), interstitial nephritis, minimal change nephropathy (See also Renal subsection in PRECAUTIONS). Dysuria, urinary urgency, hematuria, epididymitis, menorrhagia.

Laboratory Abnormalities: Elevated AST (SGOT) or ALT (SGPT), elevated alkaline phosphatase, elevated GGT, elevated LDH, elevated bilirubin, elevated serum creatinine and BUN.

DRUG ABUSE AND DEPENDENCY:

Abuse:

None reported.

Dependency:

Drug dependence has not been reported with chronic administration of mesalamine.

OVERDOSAGE:

Two cases of pediatric overdosage have been reported. A 3-year-old male who ingested 2 grams of Asacol tablets was treated with ipecac and activated charcoal; no adverse events occurred. Another 3-year-old male, approximately 16 kg, ingested an unknown amount of a maximum of 24 grams of Asacol crushed in solution (i.e., uncoated mesalamine); he was treated with orange juice and activated charcoal, and experienced no adverse events. In dogs, single doses of 6 grams of delayed-release Asacol tablets resulted in renal papillary necrosis but were not fatal. This was approximately 12.5 times the recommended human dose (based on a dose of 2.4 g/day in a 50 kg person). Single oral doses of uncoated mesalamine in mice and rats of 5000 mg/kg and 4595 mg/kg, respectively, or of 3000 mg/kg in cynomolgus monkeys, caused significant lethality.

DOSAGE AND ADMINISTRATION:

For the treatment of mildly to moderately active ulcerative colitis: The usual dosage in adults is two 400 mg tablets to be taken three times a day for a total daily dose of 2.4 grams for a duration of 6 weeks.

For the maintenance of remission of ulcerative colitis: The recommended dosage in adults is 1.6 grams daily, in divided doses. Treatment duration in the prospective, well-controlled trial was 6 months.

Two Asacol 400 mg tablets have not been shown to be bioequivalent to one Asacol® HD (mesalamine) delayed-release 800 mg tablet.

HOW SUPPLIED:

Asacol® (mesalamine) Delayed-Release Tablets are available as red-brown, capsule-shaped tablets containing 400 mg mesalamine and imprinted “0752 DR” in black.

They are supplied by State of Florida DOH Central Pharmacy as follows:

NDC | Strength | Quantity/Form | Color | Source Prod. Code
53808-0823-1 | 400 mg | 30 Tablets in a Blister Pack | red-brown | 0430-0752

Store at controlled room temperature 20° to 25°C (68° to 77°F) [see USP].

Manufactured by:
Warner Chilcott Deutschland GmbH
D-64331 Weiterstadt
Germany

Marketed by:
Warner Chilcott (US), LLC
Rockaway, NJ 07866
1-800-521-8813

Under license from Medeva Pharma Suisse AG (registered trademark owner).

U.S. Patent Nos. 5,541,170 and 5,541,171

To report SUSPECTED ADVERSE REACTIONS, contact Warner Chilcott at 1-800-521-8813 or FDA at 1-800-FDA-1088 or www.fda.gov/medwatch.

This Product was Repackaged By:

State of Florida DOH Central Pharmacy
104-2 Hamilton Park Drive
Tallahassee, FL 32304
United States

PACKAGE/LABEL PRINCIPAL DISPLAY PANEL

NDC 53808-0823-1

Asacol®

(mesalamine)

delayed-release tablets

400 mg per tablet

Not Bioequivalent to Asacol HD

Rx Only

30 Tablets

asacol.com